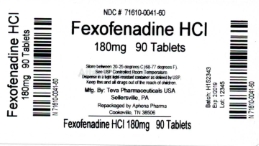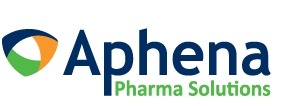 DRUG LABEL: fexofenadine hydrochloride
NDC: 71610-041 | Form: TABLET, FILM COATED
Manufacturer: Aphena Pharma Solutions - Tennessee, LLC
Category: otc | Type: HUMAN OTC DRUG LABEL
Date: 20180222

ACTIVE INGREDIENTS: FEXOFENADINE HYDROCHLORIDE 180 mg/1 1
INACTIVE INGREDIENTS: SILICON DIOXIDE; CROSCARMELLOSE SODIUM; HYPROMELLOSES; FERROSOFERRIC OXIDE; FERRIC OXIDE YELLOW; LACTOSE MONOHYDRATE; MAGNESIUM STEARATE; CELLULOSE, MICROCRYSTALLINE; POLYETHYLENE GLYCOLS; POVIDONES; TITANIUM DIOXIDE; FERRIC OXIDE RED

Perrigo Fexofenadine Hydrochloride Tablets, 180 mg Drug Facts

Active ingredient (in each tablet)

Fexofenadine HCl 180 mg

Purpose

Antihistamine

Uses

temporarily relieves these symptoms due to hay fever or other upper respiratory allergies:

- runny nose
- itchy, watery eyes
- sneezing
- itching of the nose or throat

Warnings

Do not use

if you have ever had an allergic reaction to this product or any of its ingredients.

Ask a doctor before use if you have

kidney disease. Your doctor should determine if you need a different dose.

When using this product

- do not take more than directed
- do not take at the same time as aluminum or magnesium antacids
- do not take with fruit juices (see Directions)

Stop use and ask a doctor if

an allergic reaction to this product occurs. Seek medical help right away.

If pregnant or breast-feeding,

ask a health professional before use.

Keep out of reach of children.

In case of overdose, get medical help or contact a Poison Control Center right away. (1-800-222-1222)

Directions

adults and children 12 years of age and over | take one 180 mg tablet with water once a day; do not take more than 1 tablet in 24 hours
children under 12 years of age | do not use
adults 65 years of age and older | ask a doctor
consumers with kidney disease | ask a doctor

Other information

- do not use if printed foil under cap is broken or missing
- store at 20°-25°C (68°-77°F)
- protect from excessive moisture
- this product meets the requirements of USP Dissolution Test 3

Inactive ingredients

colloidal silicon dioxide, croscarmellose sodium, hypromellose, iron oxide black, iron oxide red, iron oxide yellow, lactose monohydrate, magnesium stearate, microcrystalline cellulose, polyethylene glycol, povidone, titanium dioxide

Questions or comments?

1-800-719-9260

Repackaging Information

Please reference the How Supplied section listed above for a description of individual tablets. This drug product has been received by Aphena Pharma - TN in a manufacturer or distributor packaged configuration and repackaged in full compliance with all applicable cGMP regulations. The package configurations available from Aphena are listed below:

Count | 180 mg
30 | 71610-041-30
90 | 71610-041-60

Store between 20°-25°C (68°-77°F). See USP Controlled Room Temperature. Dispense in a tight light-resistant container as defined by USP. Keep this and all drugs out of the reach of children.

Repackaged by:
Cookeville, TN 38506
20180222DKJ

PRINCIPAL DISPLAY PANEL - 180mg

NDC 71610-041 Fexofenadine 180mg - Rx Only